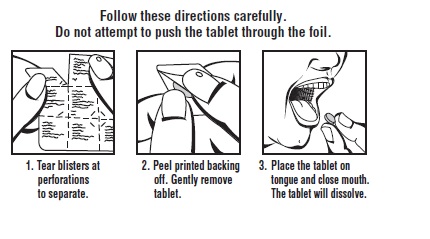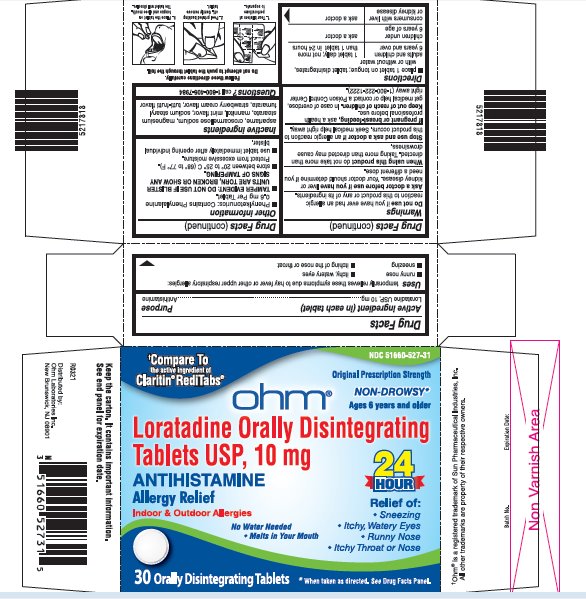 DRUG LABEL: Allergy Relief
NDC: 51660-527 | Form: TABLET, ORALLY DISINTEGRATING
Manufacturer: Ohm Laboratories Inc.
Category: otc | Type: HUMAN OTC DRUG LABEL
Date: 20210406

ACTIVE INGREDIENTS: LORATADINE 10 mg/1 1
INACTIVE INGREDIENTS: MANNITOL; CROSCARMELLOSE SODIUM; ASPARTAME; SODIUM STEARYL FUMARATE; MAGNESIUM STEARATE

Drug Facts

ACTIVE INGREDIENT (IN EACH TABLET)

Loratadine USP, 10 mg

PURPOSE

Antihistamine

USES

Temporarily relieves these symptoms due to hay fever or other upper respiratory allergies:

- runny nose
- itchy, watery eyes
- sneezing
- itching of the nose or throat

WARNINGS

Do not use

If you have ever had an allergic reaction to this product or any of its ingredients.

Ask a doctor before use if you have

Liver or kidney disease. Your doctor should determine if you need a different dose.

When using this product

Do not take more than directed. Taking more than directed may cause drowsiness.

Stop use and ask a doctor if

An allergic reaction to this product occurs. Seek medical help right away.

If pregnant or breast-feeding,

Ask a health professional before use.

Keep out of reach of children.

In case of overdose, get medical help or contact a Poison Control Center right away (1-800-222-1222).

DIRECTIONS

- place 1 tablet on tongue; tablet disintegrates, with or without water

adults and children 6 years and over | 1 tablet daily; not more than 1 tablet in 24 hours
children under 6 years of age | ask a doctor
consumers with liver or kidney disease | ask a doctor

OTHER INFORMATION

- Phenylketonurics: Contains Phenylalanine 0.6 mg Per Tablet.
- TAMPER EVIDENT: DO NOT USE IF BLISTER UNITS ARE TORN, BROKEN OR SHOW ANY SIGNS OF TAMPERING.
- store between 20° to 25° C (68° to 77° F). Protect from excessive moisture.
- use tablet immediately after opening individual blister.

INACTIVE INGREDIENTS

Aspartame, croscarmellose sodium, magnesium stearate, mannitol, mint flavor, sodium stearyl fumarate, strawberry cream flavor, tutti-frutti flavor

QUESTIONS?

Call 1-800-406-7984

PRINCIPAL DISPLAY PANEL

† Compare To the active ingredient of Claritin® RediTabs®

NDC 51660-527-31

ohm®

Original Prescription Strength

NON-DROWSY*

Ages 6 years and older

Loratadine Orally Disintegrating Tablets USP, 10 mg

ANTIHISTAMINE

Allergy Relief

Indoor & Outdoor Allergies

No Water Needed

• Melts in Your Mouth

24 HOUR

Relief of:

- Sneezing
- Itchy, Watery Eyes
- Runny Nose
- Itchy Throat or Nose

30 Orally Disintegrating Tablets

*When taken as directed. See Drug Facts Panel.

Distributed by: Ohm Laboratories Inc.

5217818/R0321